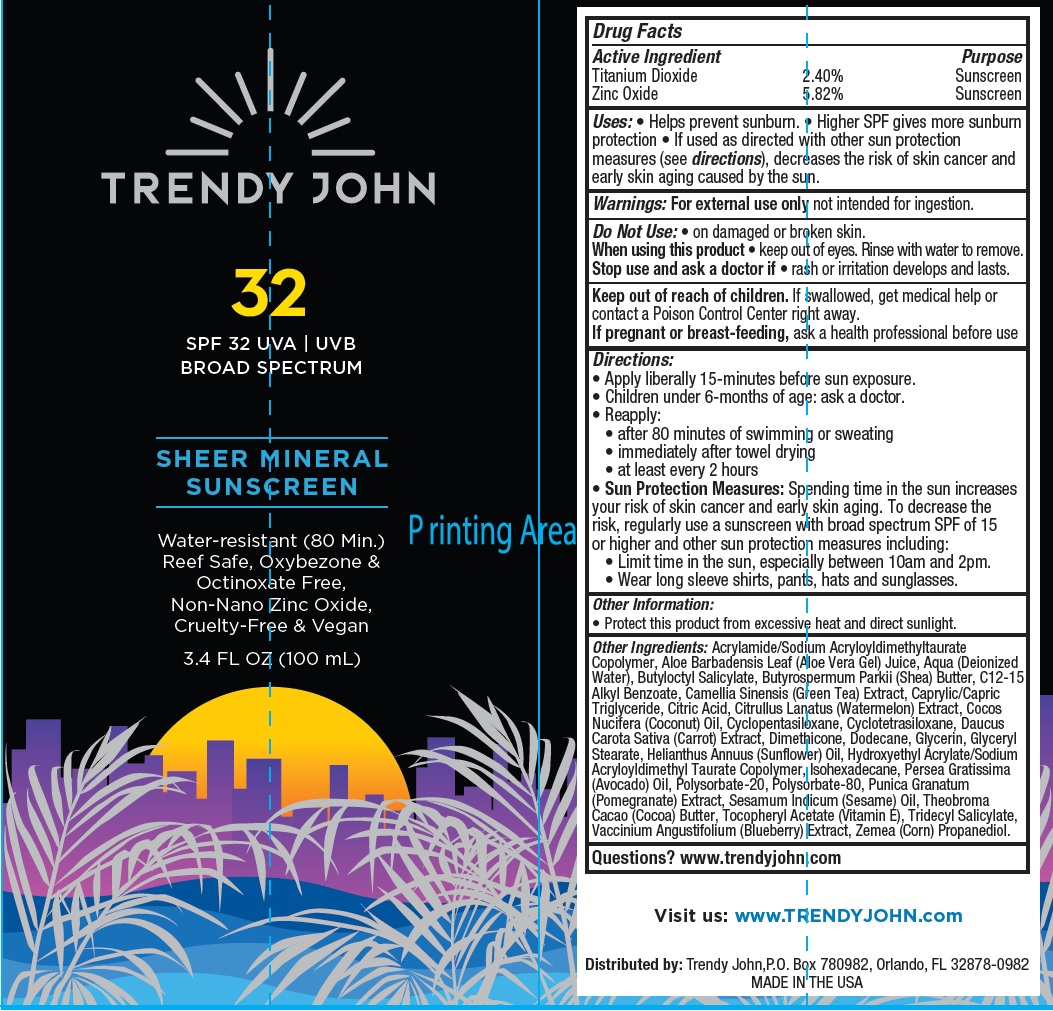 DRUG LABEL: TRENDY JOHN SPF-32 Sheer Mineral Sunscreen
NDC: 82373-248 | Form: CREAM
Manufacturer: TRENDY JOHN LLC
Category: otc | Type: HUMAN OTC DRUG LABEL
Date: 20231111

ACTIVE INGREDIENTS: TITANIUM DIOXIDE 24 mg/1 mL; ZINC OXIDE 58.2 mg/1 mL
INACTIVE INGREDIENTS: ALOE VERA LEAF; BUTYLOCTYL SALICYLATE; SHEA BUTTER; ALKYL (C12-15) BENZOATE; GREEN TEA LEAF; MEDIUM-CHAIN TRIGLYCERIDES; CITRIC ACID MONOHYDRATE; WATERMELON; COCONUT OIL; CYCLOMETHICONE 5; CYCLOMETHICONE 4; CARROT; DIMETHICONE; DODECANE; GLYCERIN; GLYCERYL MONOSTEARATE; HELIANTHUS ANNUUS FLOWERING TOP; HYDROXYETHYL ACRYLATE/SODIUM ACRYLOYLDIMETHYL TAURATE COPOLYMER (100000 MPA.S AT 1.5%); ISOHEXADECANE; AVOCADO OIL; POLYSORBATE 20; POLYSORBATE 80; PUNICA GRANATUM ROOT BARK; SESAME OIL UNSAPONIFIABLES; COCOA; .ALPHA.-TOCOPHEROL ACETATE; TRIDECYL SALICYLATE; BLUEBERRY; CORN

TRENDY JOHN SPF-32 Sheer Mineral Sunscreen

Active Ingredient

Titanium Dioxide 2.40%

Zinc Oxide 5.82%

Purpose

Sunscreen

Uses:

• Helps prevent sunburn. • Higher SPF gives more sunburn protection • If used as directed with other sun protection measures (see), decreases the risk of skin cancer and early skin aging caused by the sun. directions

Warnings:

not intended for ingestion. For external use only

Do Not Use:

• on damaged or broken skin.

When using this product

• keep out of eyes. Rinse with water to remove.

Stop use and ask a doctor if

• rash or irritation develops and lasts.

Keep out of reach of children.

If swallowed, get medical help or contact a Poison Control Center right away.

If pregnant or breast-feeding,

ask a health professional before use

Directions:

• Apply liberally 15-minutes before sun exposure. • Children under 6-months of age: ask a doctor. • Reapply: • after 80 minutes of swimming or sweating • immediately after towel drying • at least every 2 hours • Spending time in the sun increases your risk of skin cancer and early skin aging. To decrease the risk, regularly use a sunscreen with broad spectrum SPF of 15 or higher and other sun protection measures including: • Limit time in the sun, especially between 10am and 2pm. • Wear long sleeve shirts, pants, hats and sunglasses.
Sun Protection Measures:

Other Information:

• Protect this product from excessive heat and direct sunlight.

Other Ingredients:

Acrylamide/Sodium Acryloyldimethyltaurate Copolymer, Aloe Barbadensis Leaf (Aloe Vera Gel) Juice, Aqua (Deionized Water), Butyloctyl Salicylate, Butyrospermum Parkii (Shea) Butter, C12-15 Alkyl Benzoate, Camellia Sinensis (Green Tea) Extract, Caprylic/Capric Triglyceride, Citric Acid, Citrullus Lanatus (Watermelon) Extract, Cocos Nucifera (Coconut) Oil, Cyclopentasiloxane, Cyclotetrasiloxane, Daucus Carota Sativa (Carrot) Extract, Dimethicone, Dodecane, Glycerin, Glyceryl Stearate, Helianthus Annuus (Sunflower) Oil, Hydroxyethyl Acrylate/Sodium Acryloyldimethyl Taurate Copolymer, Isohexadecane, Persea Gratissima (Avocado) Oil, Polysorbate-20, Polysorbate-80, Punica Granatum (Pomegranate) Extract, Sesamum Indicum (Sesame) Oil, Theobroma Cacao (Cocoa) Butter, Tocopheryl Acetate (Vitamin E), Tridecyl Salicylate, Vaccinium Angustifolium (Blueberry) Extract, Zemea (Corn) Propanediol.

Questions?

www.trendyjohn.com